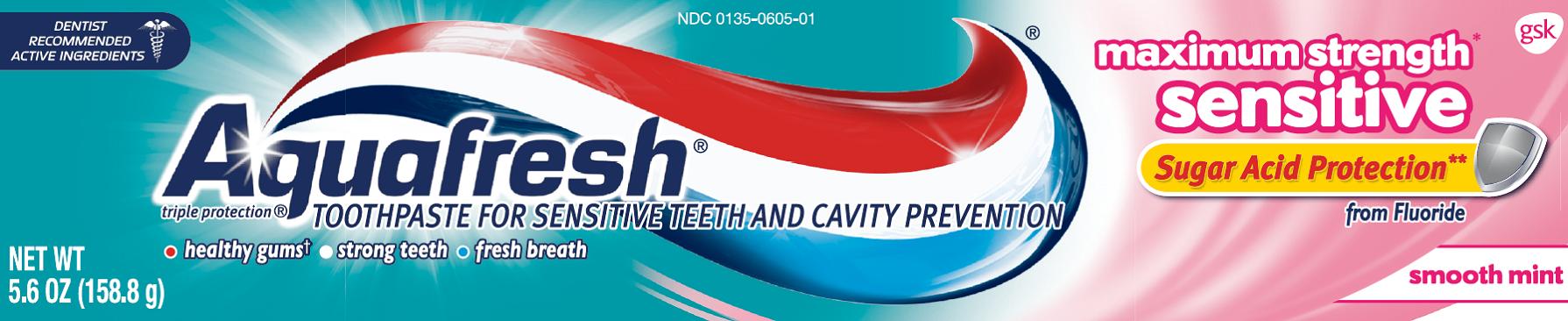 DRUG LABEL: AQUAFRESH
NDC: 0135-0605 | Form: PASTE
Manufacturer: Haleon US Holdings LLC
Category: otc | Type: HUMAN OTC DRUG LABEL
Date: 20240305

ACTIVE INGREDIENTS: POTASSIUM NITRATE 50 mg/1 g; SODIUM FLUORIDE 1.1 mg/1 g
INACTIVE INGREDIENTS: WATER; HYDRATED SILICA; SORBITOL; GLYCERIN; SODIUM LAURYL SULFATE; TITANIUM DIOXIDE; XANTHAN GUM; SACCHARIN SODIUM; SODIUM HYDROXIDE; MENTHOL, UNSPECIFIED FORM; D&C RED NO. 30; FD&C BLUE NO. 1

Drug Facts

Active ingredients

Potassium Nitrate (5%)*

Sodium fluoride 0.24% (0.15% w/v fluoride ion)

*maximum FDA sensitivity active ingredient

Purpose

Antihypersensitivity

Anticavity

Uses

- aids in the prevention of dental cavities.
- builds increasing protection against painful sensitivity of the teeth to cold, heat, acids, sweets, or contact.

Warnings

When using this product,

if irritation occurs discontinue use.

Stop use and ask a dentist if

- the problem persists or worsens. Sensitive teeth may indicate a serious problem that may need prompt care by a dentist.
- pain/sensitivity still persists after 4 weeks of use.

Keep out of reach of children.

If more than used for brushing is accidentally swallowed, get medical help or contact a Poison Control Center right away.

Directions

- adults and children 12 years of age and older:
  - apply at least a 1-inch strip of the product onto a soft bristle toothbrush.
  - brush teeth thoroughly for at least 1 minute twice a day (morning and evening), and not more than 3 times a day, or as recommended by a dentist or doctor. Make sure to brush all sensitive areas of the teeth. Minimize swallowing. Spit out after brushing.
- children under 12 years of age: Consult a dentist or doctor.

Other information

- store below 30°C (86°F)

Inactive ingredients

water, hydrated silica, sorbitol, glycerin, sodium lauryl sulfate, flavor, titanium dioxide, xanthan gum, sodium saccharin, sodium hydroxide, menthol, red 30, blue 1

Questions or comments?

Call toll-free 1-800-897-5623

Principal Display Panel

NDC 0135-0605-01

Aquafresh®

TOOTHPASTE FOR SENSITIVE TEETH AND CAVITY PREVENTION

triple protection®

DENTIST RECOMMENDED ACTIVE INGREDIENTS

maximum strength* sensitive

Sugar Acid Protection**

from Fluoride

- healthy gums†
- strong teeth
- fresh breath

smooth mint

NET WT 5.6 OZ (158.8 g)

Aquafresh® Maximum Strength* Sensitive toothpaste cares for your mouth, helping you keep it healthy and happy. With regular use, you can once again enjoy your favorite foods without the nagging pain of sensitive teeth.

**With Sugar Acid Protection provided by fluoride, which strengthens enamel, creating a shield that protects the tooth surface against sugar acid attack.

targets the source of Sensitive tooth pain, soothes the nerves and reduces painful sensitivity

†with twice daily brushing

ALWAYS FOLLOW THE LABEL

Trademarks are owned by or licensed of the GSK group of companies.

GSK Consumer Healthcare Warren, NJ 07059

*maximum FDA sensitivity active ingredient

©2015 GSK or its licensor.

105481XA